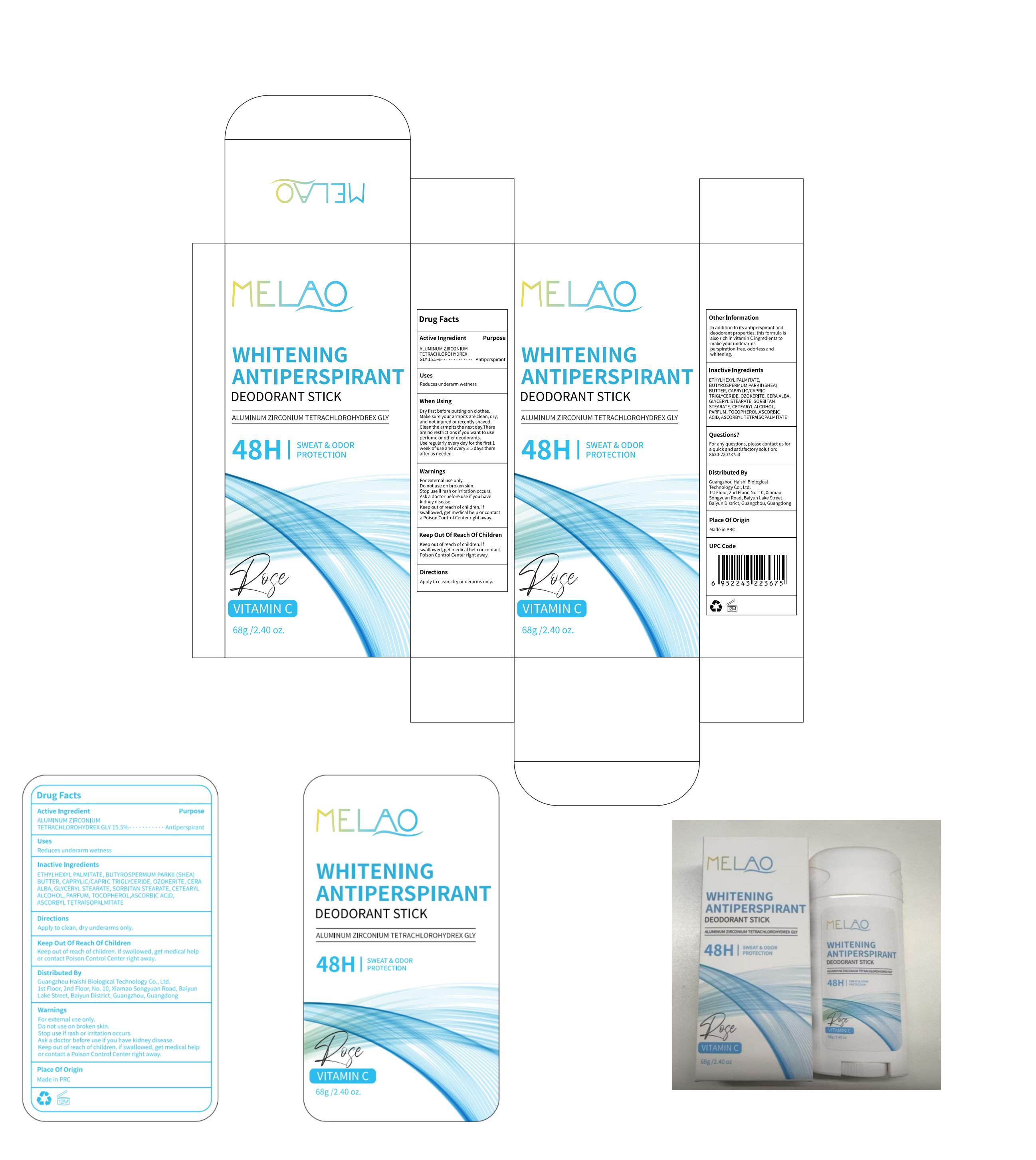 DRUG LABEL: MELAO Whitening Antiperspirant Deodorant Stick (rose)
NDC: 60771-0014 | Form: STICK
Manufacturer: Guangzhou Haishi Biological Technology Co., Ltd.
Category: otc | Type: HUMAN OTC DRUG LABEL
Date: 20250526

ACTIVE INGREDIENTS: ALUMINUM ZIRCONIUM TETRACHLOROHYDREX GLY 15.5 g/100 g
INACTIVE INGREDIENTS: CETEARYL ALCOHOL; ASCORBYL TETRAISOPALMITATE; GLYCERYL STEARATE; TOCOPHEROL; ETHYLHEXYL PALMITATE; CAPRYLIC/CAPRIC TRIGLYCERIDE; SORBITAN STEARATE; ASCORBIC ACID

MELAO WHITENING ANTIPERSPIRANT DEODORANT STICK (ROSE)

PURPOSE

Antiperspirant

ACTIVE INGREDIENT

ALUMINUM ZIRCONIUM TETRACHLOROHYDREX GLY 15.5%

INDICATIONS AND USAGE

DIRECTION:Spin out the paste, apply evenly under thearmpit.

Ask a doctor before use if you have kidney disease.

if swallowed, get medical help or contact a Poison Control Center right away.

Stop use if rash or irritation occurs.

Do not use on broken skin.

WHEN USING

Dry first before putting on clothes.Make sure your armpits are clean, dry,and not iniured or recently shaved.Clean the armpits the next day.Thereare no restrictions if you want to use perfume or other deodorants.keep out of eyes.

Keep out of reach of children

DOSAGE AND ADMINISTRATION

Use regularly every day for the first 1week of use and every 3-5 days thereafter as needed.

INACTIVE INGREDIENT

OZOKERITE10%
CETEARYL ALCOHOL4%
BUTYROSPERMUM PARKII (SHEA BUTTER)18%
CAPRYLIC/CAPRIC TRIGLYCERIDE10%
ETHYLHEXYL PALMITATE24.8%
GLYCERYL STEARATE4%
SORBITAN STEARATE4%
CERA ALBA6%
ASCORBIC ACID0.5%
TOCOPHEROL1%
ASCORBYL TETRAISOPALMITATE0.2%
PARFUM2%